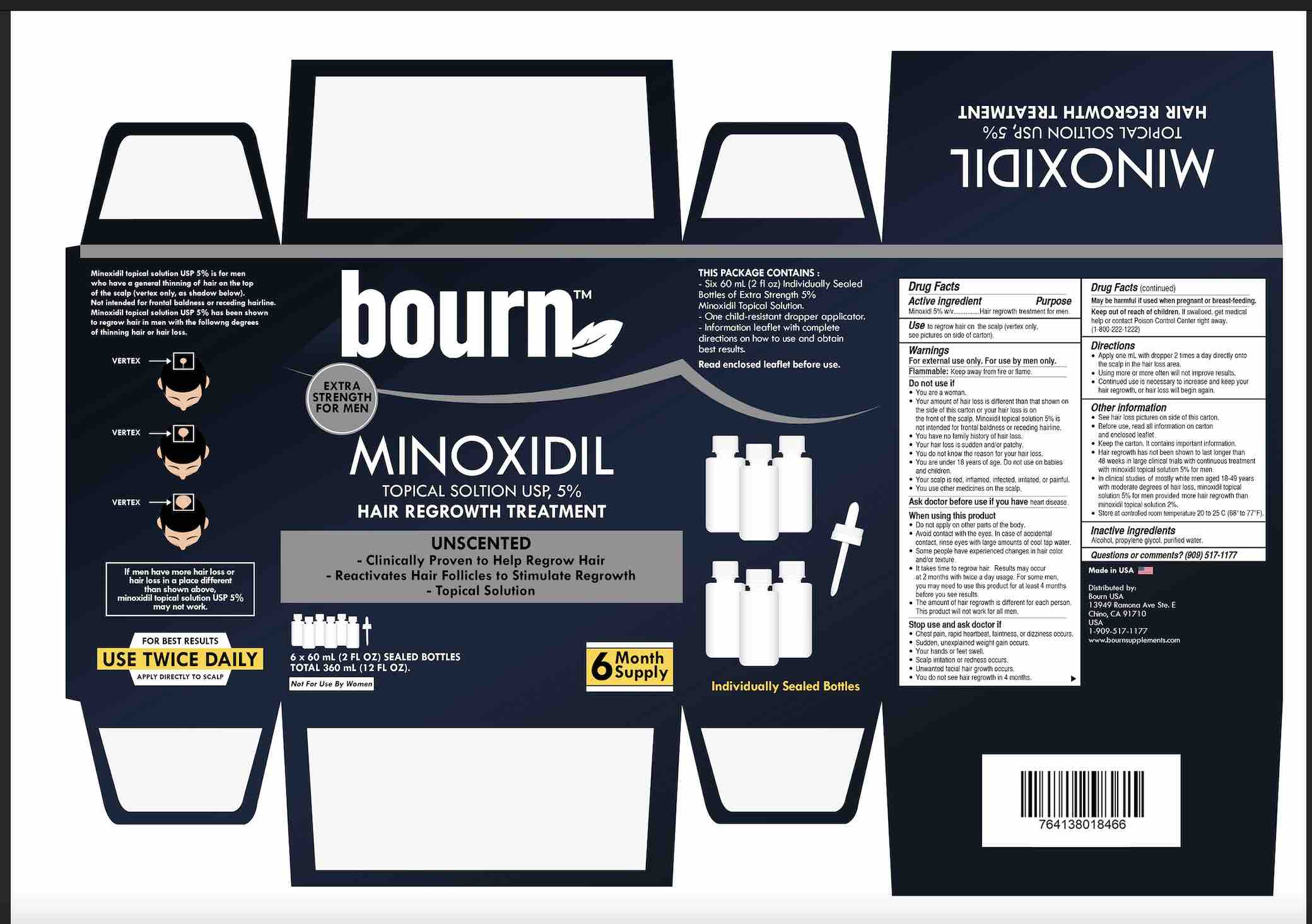 DRUG LABEL: bourn Hair Regrowth Treatment for Men
NDC: 81553-001 | Form: SOLUTION
Manufacturer: Octri, Inc.
Category: otc | Type: HUMAN OTC DRUG LABEL
Date: 20230110

ACTIVE INGREDIENTS: MINOXIDIL 5 g/100 mL
INACTIVE INGREDIENTS: ISOPROPYL ALCOHOL; WATER; PROPYLENE GLYCOL

bourn Minoxidil Topical Solution, USP 5% - Hair Regrowth Treatment for Men

ACTIVE INGREDIENT

Minoxidil 5% w/v

PURPOSE

Hair regrowth treatment for men

USE

to regrow hair on the top of the scalp (vertex only, see pictures on side of carton)

WARNINGS

For external use only. For use by men only.

Flammable: Keep away from fire or flame

Do not use if

■ You are a woman

■ Your amount of hair loss is dierent than that shown on the side of this carton, or your hair loss is on the front of the scalp.

Minoxidil topical solution 5% is not intended for frontal baldness or receding hairline.

■ You have no family history of hair loss

■ Your hair loss is sudden and/or patchy

■ You do not know the reason for your hair loss

■ You are under 18 years of age. Do not use on babies and children.

■ Your scalp is red, inflamed, infected, irritated, or painful

■ You use other medicines on the scalp

Ask a doctor before use if you have heart disease

When using this product

■ Do not apply on other parts of the body

■ Avoid contact with the eyes. In case of accidental contact, rinse eyes with large amounts of cool tap water.

■ Some people have experienced chances in hair color and/or texture

■ It takes time to regrow hair. Results may occur at 2 months with twice a day usage. For some men, you may need to use this product

for at least 4 months before you see results.

■ The amount of hair regrowth is different for each person. This product will not work for all men.

Stop use and ask a doctor if

■ Chest pain, rapid heartbeat, faintness, or dizziness occurs

■ Sudden, unexplained weight gain occurs

■ Your hands or feet swell

■ Scalp irritation or redness occurs

■ Unwanted facial hair growth occurs

■ You do not see hair regrowth in 4 months

PREGNANCY OR BREAST FEEDING

May be harmful if used when pregnant or breast-feeding.

Keep out of reach of children. If swallowed, get medical help or contact a Poison Control Center right away. (1-800-222-1222)

DIRECTIONS

- apply 1 mL with dropper 2 times a day directly onto the scalp in the hair loss area
- using more or more often will not improve results
- continued use is necessary to increase and keep your hair regrowth, or hair loss will begin again

OTHER INFORMATION

• see hair loss pictures on side of this carton

• before use, read all information on carton and enclosed leaflet

• keep the carton. It contains important information.

• hair regrowth has not been shown to last longer than 48 weeks in large clinical trials with

continuous treatment with 5% minoxidil topical solution for men

•in clinical studies of mostly white men aged 18-49 years with moderate degrees of hair loss, minoxidil topical solution 5%

for men provided more hair regrowth than minoxidil topical solution 2%

• store at controlled room temperature 20º to 25ºC (68º to 77ºF)

INACTIVE INGREDIENT

alcohol, propylene glycol, purified water

Questions or comments? (909) 517-1177